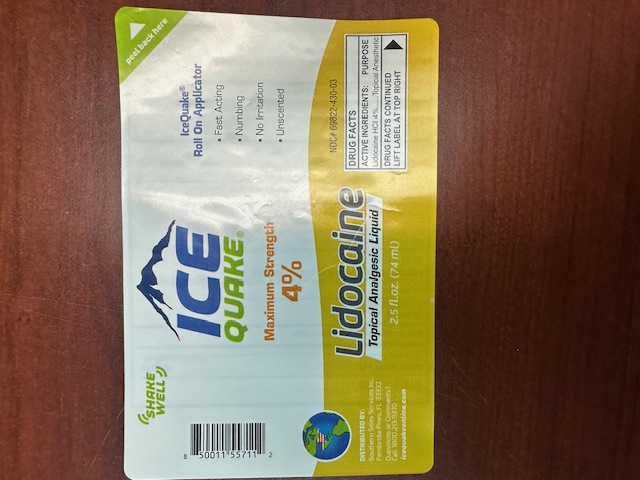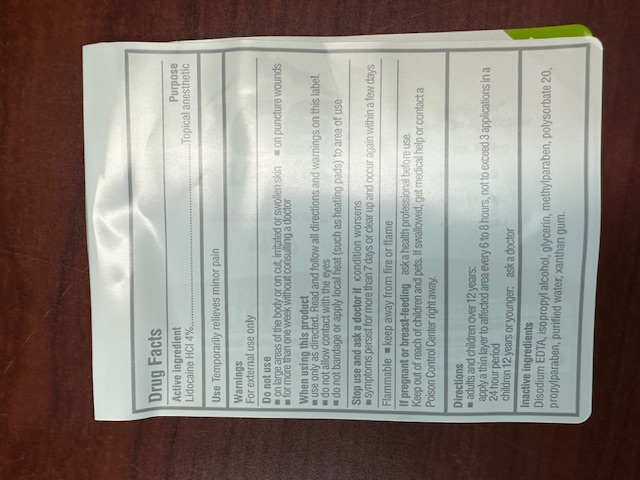 DRUG LABEL: IceQuake Lidocaine Analgesic
NDC: 65852-026 | Form: LIQUID
Manufacturer: Dextrum Laboratories, Inc
Category: otc | Type: HUMAN OTC DRUG LABEL
Date: 20251121

ACTIVE INGREDIENTS: LIDOCAINE 4 g/100 mL
INACTIVE INGREDIENTS: EDETATE DISODIUM; ISOPROPYL ALCOHOL; GLYCERIN; WATER; XANTHAN GUM; POLYSORBATE 20; METHYLPARABEN; PROPYLPARABEN

IceQuake Lidocaine Analgesic

ACTIVE INGREDIENTS:

Lidocaine HCI 4%

PURPOSE

Topical Anesthetic

Do not use

- on large areas of the body or on cut, irritated or swollen skin a on puncture wounds
- for more than one week without consulting a doctor

When using this product

- use only as directed. Read and follow all directions and warnings on this label.
- do not allow contact with the eyes
- do not bandage or apply local heat (such as heating pads) to area of use

Stop use and ask a doctor if condition worsens

- symptoms persist for more than 7 days or clear up and occur again within a few days

Warnings

For external use only

Indication & usage section

Use Temporarily relieves minor pain

• adults and children over 12 years:

apply a thin layer to affected area every 6 to 8 hours, not to exceed 3 applications in a 24 hour period

- children 12 years or younger: ask a doctor

PREGNANCY OR BREAST FEEDING

iF pregnant or breast-feeding ask a health professional before use.

Keep out of reach of children and pets.

If swallowed, get medical help or contact a Poison Control Center right away.

Inactive ingredients

Disodium EDTA, isopropyl alcohol, glycerin, methylparaben, polysorbate 20, propylparaben, purified water, xanthan gum.

DOSAGE AND ADMINISTRATION:

• adults and children over 12 years:

apply a thin layer to affected area every 6 to 8 hours, not to exceed 3 applications in a 24 hour period

- children 12 years or younger: ask a doctor

PACKAGE LABEL

ICE

QUAKE

Maximum Strength

4%. peel back here

Lidocaine

Topical Analgesic Liquid

2.5 fl.oz. (74 ml)

IceQuake®

Roll On Applicator

- Fast Acting
- Numbing
- No Irritation
- Unscented

NDC# 69822-430-03

DRUG FACTS

ACTIVE INGREDIENTS: PURPOSE

Lidocaine HCI 4%....... Topical Anesthetic

DRUG FACTS CONTINUED LIFT LABEL AT TOP RIGHT